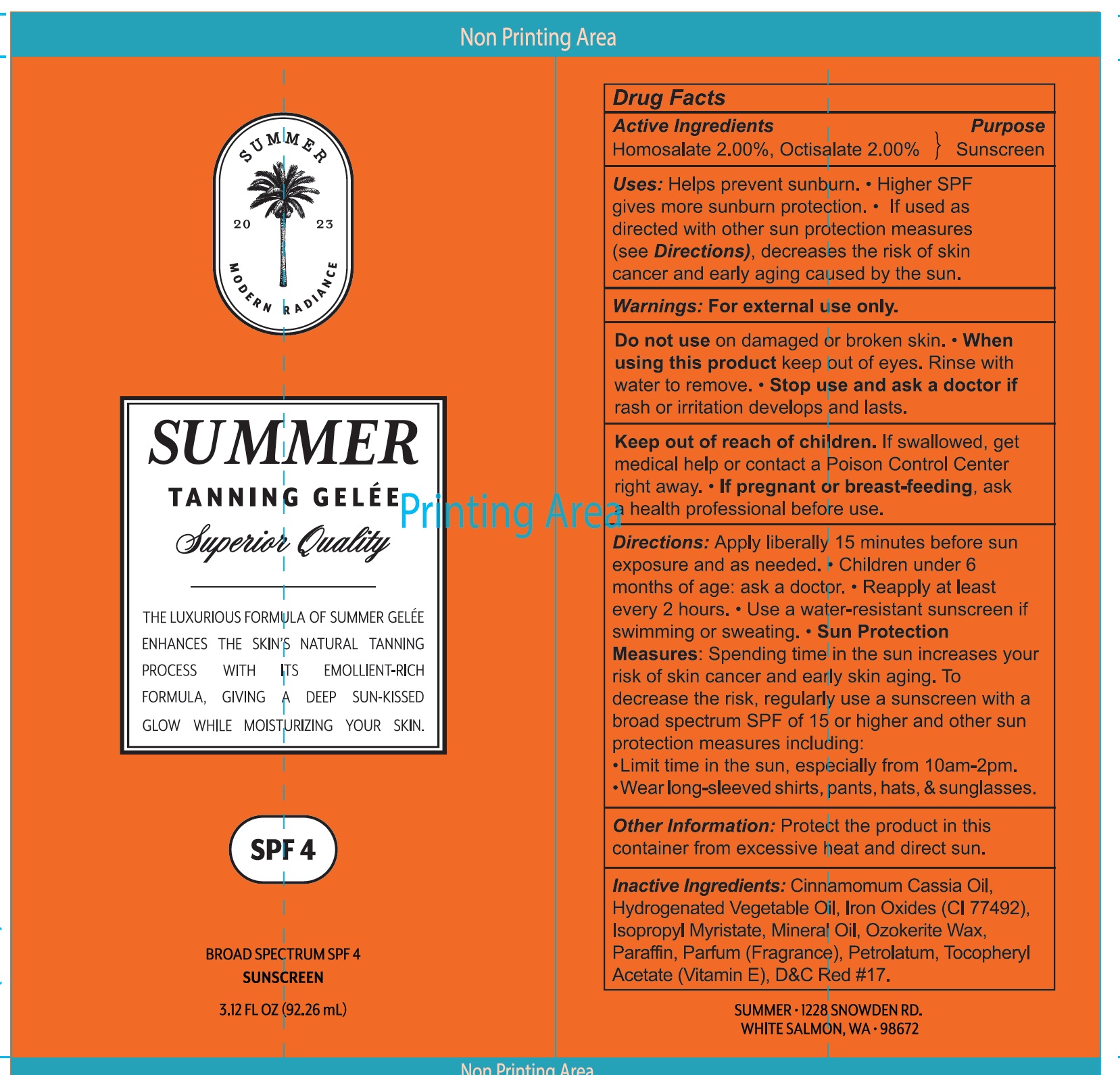 DRUG LABEL: SUMMER GELEE SPF-4
NDC: 84281-476 | Form: GEL
Manufacturer: SUMMER GELEE LLC
Category: otc | Type: HUMAN OTC DRUG LABEL
Date: 20240427

ACTIVE INGREDIENTS: HOMOSALATE 20 mg/1 mL; OCTISALATE 20 mg/1 mL
INACTIVE INGREDIENTS: CHINESE CINNAMON OIL; FERRIC OXIDE RED; ISOPROPYL MYRISTATE; MINERAL OIL; CERESIN; PARAFFIN; PETROLATUM; .ALPHA.-TOCOPHEROL ACETATE; D&C RED NO. 17

SUMMER GELEE SPF-4

Active Ingredients

Homosalate 2.00%, Octisalate 2.00%

Purpose

Sunscreen

Uses:

Helps prevent sunburn.

- Higher SPF gives more sunburn protection.
- If used as directed with other sun protection measures (see Directions), decreases the risk of skin cancer and early aging caused by the sun.

Warnings:

For external use only.

Do not use

on damaged or broken skin.

When using this product

- keep out of eyes. Rinse with water to remove.

Stop use and ask a doctor if

- rash or irritation develops and lasts.

Keep out of reach of children.

If swallowed, get medical help or contact a Poison Control Center right away.

If pregnant or breast-feeding,

ask a health professional before use.

Directions:

Apply liberally 15 minutes before sun exposure and as needed.

- Children under 6 months of age: ask a doctor.
- Reapply at least every 2 hours.
- Use a water-resistant sunscreen if swimming or sweating.
- Sun Protection Measures: Spending time in the sun increases your risk of skin cancer and early skin aging. To decrease the risk, regularly use a sunscreen with a broad spectrum SPF of 15 or higher and other sun protection measures including:
- Limit time in the sun, especially from 10am-2pm.
- Wear long-sleeved shirts, pants, hats, & sunglasses.

Other Information:

Protect the product in this container from excessive heat and direct sun.

Inactive Ingredients:

Cinnamomum Cassia Oil, Hydrogenated Vegetable Oil, Iron Oxides (CI 77492), Isopropyl Myristate, Mineral Oil, Ozokerite Wax, Paraffin, Parfum (Fragrance), Petrolatum, Tocopheryl Acetate (Vitamin E), D&C Red #17.